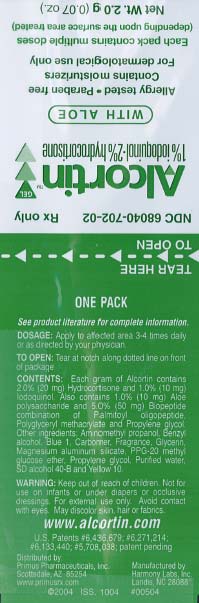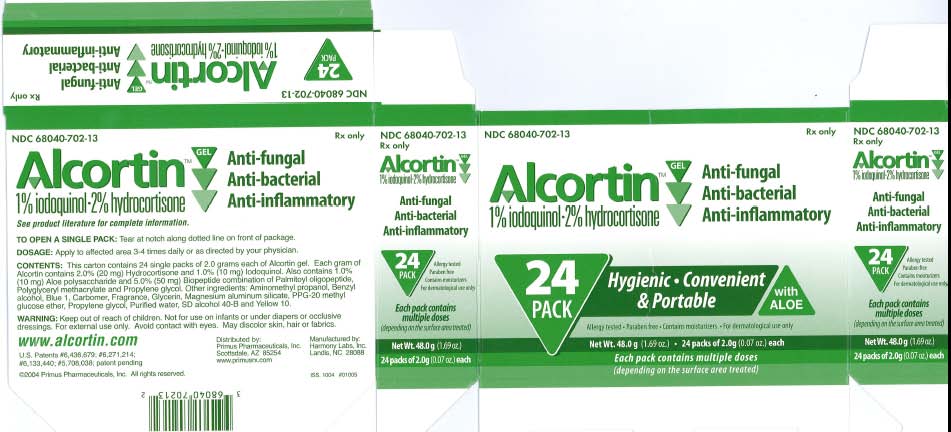 DRUG LABEL: Alcortin
NDC: 68040-702 | Form: GEL
Manufacturer: Primus Pharmaceuticals
Category: prescription | Type: HUMAN PRESCRIPTION DRUG LABEL
Date: 20100421

ACTIVE INGREDIENTS: Hydrocortisone 2 g/100 g; IODOQUINOL 1 g/100 g

Alcortin 1% iodoquinol - 2% hydrocortisone with Aloe

Alcortin 2.0 g ucarton.jpg

NDC 68040-702-13 Rx only
Alcortin
Anti-fungal
Anti-bacterial
Anti-inflammatory
1% Iodoquinol 2% Hydrocortisone
See product literature for complete information.
TO OPEN A SINGLE PACK: Tear at notch along dotted line on front of package.
DOSAGE: Apply to affected area 3-4 times daily or as directed by your physician.
CONTENTS: This carton contains 24 single packs of 2.0 grams each of Alcortin gel. Each gram of
Alcortin contains 2.0% (20 mg) Hydrocortisone and 1.0% (10 mg) lodoquinol. Also contains 1.0%
(10 mg) Aloe polysaccharide and 5.0% (50 mg) Biopeptide combination of Palmitoyl oligopeptide,
Polyglyceryl methacrylate and Propylene glycol. Other ingredients: Aminomethyl propanol, Benzyl
alcohol, Blue 1, Carbomer, Fragrance, Glycerin, Magnesium aluminum silicate, PPG-20 methyl
glucose ether, Propylene glycol, Purified water, SO alcohol 40-B and Yellow 10.
WARNING: Keep out of reach of children. Not for use on infants or under diapers or occlusive
dressings. For external use only. Avoid contact with eyes. May discolor skin, hair or fabrics.
www.alcortin.com
U.S. Patents #6,436,679; #6,271 ,214;
#6,133,440; #5,708,038; patent pending
2004 Primus Pharmaceuticals, Inc. All rights reserved.
Distributed by:
Primus Pharmaceuticals, Inc.
Scottsdale, AZ 85254
www.primusrx.com
Manufactured by:
Harmony Labs, Inc.
Landis, NC 28088
NDC 68040-702-13
Rx only
Alcortin
1% iodoquinol - 2% hydrocrtisone
Anti-fungal
Anti-bacterial
Anti-inflammatory
24 PACK
Allergy tested
Paraben free
Contains moisturizers
For dermatological use only
Each pack contains
multiple doses
(depending on the surface area treated)
NetWt 48.0g(1.69 oz)
24 packs of 2.0g(0.07 oz) each
NDC 68040-702-13
Alcortin
1% iodoquinol - 2% hydrocrtisone
Rx only
Anti-fungal
Anti-bacterial
Anti-inflammatory
NDC 68040-702-13
Rx only
Alcortin
1% iodoquinol - 2% hydrocrtisone
Anti-fungal
Anti-bacterial
Anti-inflammatory
Paraben free
Contains moisturizers
For dermatological use only
Each pack contains
multiple doses
NetWt 48.0g(1.69 oz)
24 packs of 2.0g(0.07 oz) each
multiple doses
(depending on the surface area treated)

Alcortin 2 g packet.jpg

NDC 68040-702-02 Rx only
Alcortin gel 1% iodoquinol - 2% hydrocortisone with Aloe
Allergy tested - Paraben free
Contains moisturizers
For dermatological use only
Each pack contains multiple doses(depending upon the surface area treated)
NetWt. 2.0 g (0.07oz)
See product literature for complete information.
Dosage: Apply to affect area 3-4 times daily or as directed by your physician.
To Open: Tear at notch along dotted line on front of package.
Contents: Each gram of Alcortin contains 2.0% (20 mg Hydrocortisone and 1.0% (10 mg) Iodoquinol.
Also contains 1.0% (10 mg) Aloe polysaccharide and 5.0% (50 mg) Biopeptide combination of Palmitoyl oligopeptide, Poyglyceryl methacrylate and Propylene glycol. Other ingredients: Aminomethyl propanol, Benzyl alcohol, Blue 1, Carbomer, Fragrance, Glycerin, Magnesium aluminum silicate, PPG-20 methyl glucose ether, Propylene glycol, Purified water, SD alcohol 40-B and Yellow 10.
Warning: Keep out of reach of children. Not for use on infants or under diapers or occlusive dressings. For external use only. Avoid contact with eyes. May discolor skin, hair or fabrics.
www.alcortin.com
Distributed by: Primus Pharmaceuticals, Inc.
Scottsdale, AZ 85254
Manufactured by: Harmony Labs, Inc.
Landis, NC 28088
U.S. Patents #6,436,679; #6,271,214; #6,133,440; #5,708,038; patent pending

Insert

Prescribing Information
ALCORTINgel
DESCRIPTION
Each gram of Alcortin contains 2.0% (20 mg)
Hydrocortisone and 1.0% (10 mg) lodoquinol.
Also contains 1.0% (10 mg) Aloe polysaccharide
and 5.0% (50 mg) Biopeptide combination
of Palmitoyloligopeptide, Polyglycerylmethacrylate
and Propylene glycol. Other
ingredients: Aminomethyl propanol, Benzyl
alcohol, Blue 1, Carbomer, Fragrance, Glycerin,
Magnesium aluminum silicate, PPG-20 methyl
glucose ether, Propylene glycol, Purified water,
SO alcohol 40-B and Yellow 10.
lodoquinol
lodoquinol is an antifungal and antibacterial
agent. Chemically, lodoquinol is [5,7-diiodo-8-
quinolinol] with the molecular formula
(C9HsI2NO)
Hydrocortisone
Hydrocortisone is an anti-inflammatory and
antipruritic agent. Chemically, hydrocortisone is
[Pregn-4-ene-3, 20-dione, 11, 17, 21- trihydroxy-,
(11 B)-] with the molecular formula
(C21H300s)
CLINICAL PHARMACOLOGY
Hydrocortisone has anti-inflammatory, antipruritic
and vasoconstrictive properties. While the
mechanism of anti-inflammatory activity is
unclear, there is evidence to suggest that a recognizable
correlation exists between vasoconstrictor
potency and therapeutic efficacy in
humans. lodoquinol has both antifungal and
antibacterial properties.
Pharmacokinetics
The extent of percutaneous absorption of topical
steroids is determined by many factors
including the vehicle, the integrity of the epidermal
barrier and the use of occlusive dressings.
Hydrocortisone can be absorbed from normal
intact skin. Inflammation and/or other inflammatory
disease processes in the skin increase
percutaneous absorption. Occlusive dressings
substantially increase the percutaneous
absorption of topical corticosteroids. Once
absorbed throuah the skin. hvdrocortisone is
tetrahydrocortisone and tetrahydrocortisol.
These are excreted in the urine, mainly conjugated
as glucuronides, together with a very
small proportion of unchanged hydrocortisone.
There are no data available regarding the percutaneous
absorption of iodoquinol; however,
following oral administration, 3-5% of the dose
was recovered in the urine as a glucuronide.
INDICATIONS AND USAGE
Based on a review of a related drug by the
National Research Council and subsequent
FDA classification for that drug, the indications
are as follows: "Possibly" Effective: Contact or
atopiC dermatitis; impetiginized eczema; nummular
eczema; endogenous chronic infectious
dermatitis; stasis dermatitis; pyoderma; nuchal
eczema and chronic eczematoid otitis externa;
acne urticata; localized or disseminated neurodermatitis;
lichen simplex chronicus; anogenital
pruritus (vulvae, scroti, ani); folliculitis; bacterial
dermatoses; mycotic dermatoses such as tinea
(capitis, cruris, corporis, pedis); monliasis; intertrigo.
Final classification of the less-than-effective
indications requires further investigation.
CONTRAINDICATIONS
Alcortin is contraindicated in those patients with
a history of hypersensitivity to hydrocortisone,
iodoquinol, aloe vera, glycine, histidine, lysine,
palmitic acid or any other components of the
preparation.
WARNINGS AND PRECAUTIONS
For external use only. Keep away from eyes. If
irritation develops, the use of Alcortin should be
discontinued and appropriate therapy instituted.
Staining of the skin, hair and fabrics may occur.
Not intended for use on infants or under diapers
or occlusive dressings. If extensive areas are
treated or if the occlusive dressing technique is
used, the possibility exists of increased systemic
absorption of the corticosteroid, and suitable
precautions should be taken. Children may
absorb proportionally larger amounts of topical
corticosteroids and thus be more susceptible to
systemic toxicity. Parents of pediatric patients
should be advised not to use tight-fitting diapers
or plastic pants on a child being treated in the
diaper area, as these garments may constitute
occlusive dressings. lodoquinol may be
absorbed through the skin and interfere with
thyroid function tests. If such tests are contemplated,
wait at least one month after discontinuance
of therapy to perform these tests. The ferric
chloride test for phenylketonuria (PKU) can
yield a false positive res!Jlt if iodoquinol is present
in the diaper or urine. Prolonged use may
result in overgrowth of non-susceptible organisms
requiring appropriate therapy. Keep out of
reach of children. Burning, itching, irritation and
dryness have been reported infrequently following
the use of topical corticosteroids.
Carcinogenesis, Mutagenisis and Impairment of
Fertility: Long term animal studies have not
been performed to evaluate the carcinogenic
potential of the effect on fertility of hydrocortinegative
results. Mutagenicity studies have not
been performed with iodoquinol.
Pregnancy Category C: Animal reproductive
studies have not been conducted with Alcortin.
It is not known whether Alcortin can cause fetal
harm when administered to pregnant women or
can affect reproductive capacity. Alcortin
should be given to pregnant women only if
clearly needed.
Nursing Mothers: It is not known whether this
drug is excreted in human milk. Because many
drugs are excreted in human milk, caution
should be exercised when Alcortin is administered
to a nursing woman.
Pediatric Use: Safety and effectiveness in pediatric
patients under the age of 12 have not been
established.
ADVERSE REACTIONS
The following local adverse reactions are
reported infrequently with topical corticosteroids.
These reactions are listed in an approximate
decreasing order of occurrence. Burning,
itching, irritation, dryness, folliculitis, hypertrichosis,
acneiform eruptions, hypopigmentation,
perioral dermatitis, allergic contact dermatitis,
maceration of the skin, secondary infections,
skin atrophy, striae and miliaria.
DOSAGE AND ADMINISTRATION
Apply to affected area 3-4 times daily in accordance
with physician's directions or as directed
otherwise by a physician.
HOW SUPPLIED
FORM NDC # 68040-702-13 .
48.0 gram carton of 24-count of 2.0 gram gel individual packs
FORM NDC # 68040-702-02
2.0 gram gel individual pack
FORM NDC # 68040-702-08
10 count carton of 2.0 gram gel sample packs - not for resale
Each 2.0 gram gel pack contains multiple doses
depending on the surface area treated.
STORAGE
Store at room temperature 15°-30°C (59°-86°F).
Keep tightly closed.
Rx only www.alcortin.com
U.S. Patents
#6,436,679; #6,271 ,214; #6,133,440;
#5,708,038; patent pending
Manufactured for:
Primus Pharmaceuticals, Inc.
Scottsdale, AZ 85254
www.primusrx.com